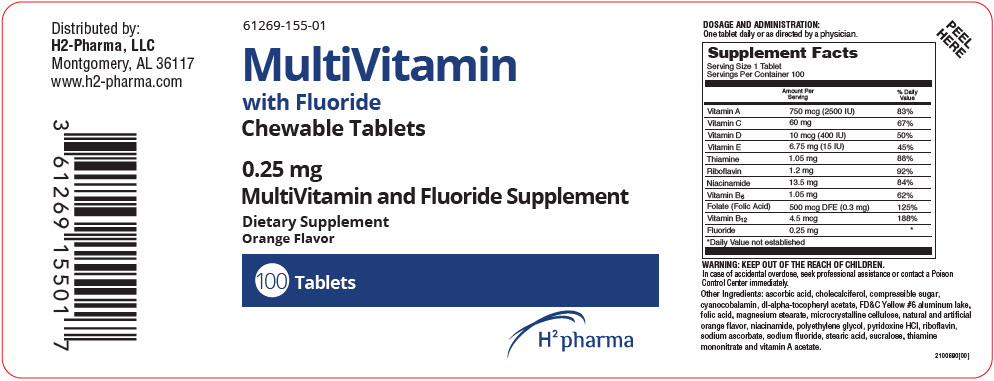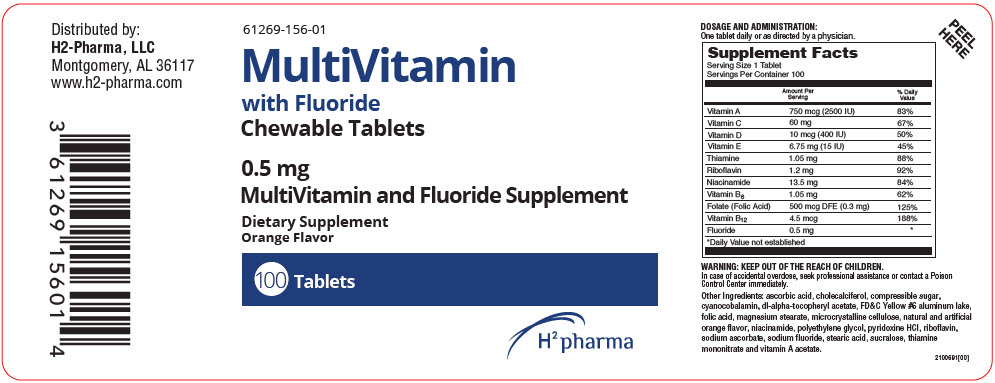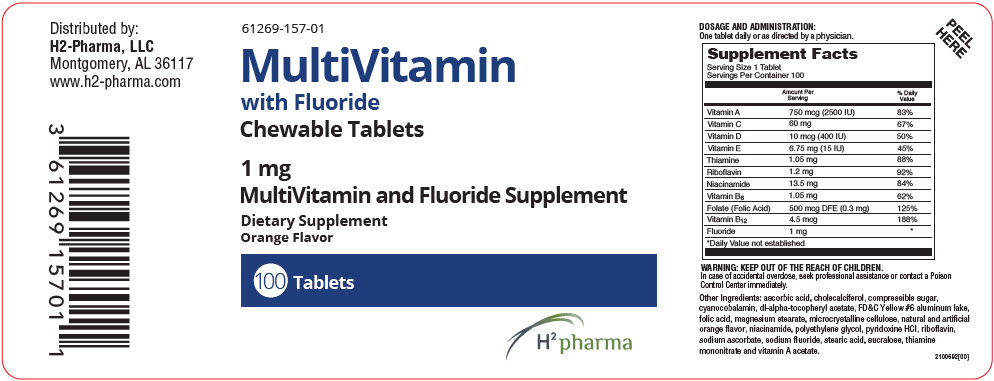 DRUG LABEL: MultiVitamin with Fluoride
NDC: 61269-155 | Form: TABLET, CHEWABLE
Manufacturer: H2-Pharma, LLC
Category: other | Type: DIETARY SUPPLEMENT
Date: 20250916

ACTIVE INGREDIENTS: VITAMIN A ACETATE 750 ug/1 1; ASCORBIC ACID 60 mg/1 1; CHOLECALCIFEROL 10 ug/1 1; .ALPHA.-TOCOPHEROL ACETATE, DL- 6.75 mg/1 1; THIAMINE MONONITRATE 1.05 mg/1 1; RIBOFLAVIN 1.2 mg/1 1; NIACINAMIDE 13.5 mg/1 1; PYRIDOXINE HYDROCHLORIDE 1.05 mg/1 1; FOLIC ACID 500 ug/1 1; CYANOCOBALAMIN 4.5 ug/1 1; SODIUM FLUORIDE 0.25 mg/1 1
INACTIVE INGREDIENTS: SUCROSE; FD&C YELLOW NO. 6; MAGNESIUM STEARATE; MICROCRYSTALLINE CELLULOSE; POLYETHYLENE GLYCOL, UNSPECIFIED; SODIUM ASCORBATE; STEARIC ACID; SUCRALOSE

MultiVitamin
with Fluoride
Chewable Tablets

DOSAGE AND ADMINISTRATION

One tablet daily or as directed by a physician.

STATEMENT OF IDENTITY

Supplement Facts
Serving Size 1 Tablet
Servings Per Container 100
 | Amount Per Serving | % Daily Value
Vitamin A | 750 mcg (2500 IU) | 83%
Vitamin C | 60 mg | 67%
Vitamin D | 10 mcg (400 IU) | 50%
Vitamin E | 6.75 mg (15 IU) | 45%
Thiamine | 1.05 mg | 88%
Riboflavin | 1.2 mg | 92%
Niacinamide | 13.5 mg | 84%
Vitamin B6 | 1.05 mg | 62%
Folate (Folic Acid) | 500 mcg DFE (0.3 mg) | 125%
Vitamin B12 | 4.5 mcg | 188%
Fluoride | 0.25 mg | [Daily Value not established]

WARNING

KEEP OUT OF THE REACH OF CHILDREN.

In case of accidental overdose, seek professional assistance or contact a Poison Control Center immediately.

HEALTH CLAIM

Other Ingredients: ascorbic acid, cholecalciferol, compressible sugar, cyanocobalamin, dl-alpha-tocopheryl acetate, FD&C Yellow #6 aluminum lake, folic acid, magnesium stearate, microcrystalline cellulose, natural and artificial orange flavor, niacinamide, polyethylene glycol, pyridoxine HCl, riboflavin, sodium ascorbate, sodium fluoride, stearic acid, sucralose, thiamine mononitrate and vitamin A acetate.

Active ingredient for caries prophylaxis: Fluoride as sodium fluoride.

CLINICAL PHARMACOLOGY

Significant decrease in the incidence of dental caries can be linked to the fluoridation of the water supply (1ppm fluoride) during the period of tooth development.

MultiVitamin with Fluoride Chewable Tablets provide sodium fluoride and ten essential vitamins in a chewable tablet. Because the tablets are chewable, they provide a topical as well as systemic source of fluoride. Hydroxyapatite is the principal crystal for all calcified tissue in the human body. The fluoride ion reacts with the hydroxyapatite in the tooth as it is formed to produce the more caries-resistant crystal fluorapatite.

The reaction may be expressed by the equation:

Ca10(PO4)6(OH2) + 2F- |  | Ca10 (PO4)6F2 + 2OH-
(Hydroxyapatite) |  | (Fluorapatite)

Three stages of fluoride deposition in tooth enamel can be distinguished:

1. Small amounts (reflecting the low levels of fluoride in tissue fluids) are incorporated into the enamel crystals while they are being formed.

2. After enamel has been laid down, fluoride deposition continues in the surface enamel. Diffusion of fluoride from the surface inward is apparently restricted.

3. After eruption, the surface enamel acquires fluoride from the water, food, supplementary fluoride and smaller amounts of saliva.

DIETARY SUPPLEMENTATION

MultiVitamins with Fluoride Chewable Tablets offer supplementation of the diet with 10 vitamins and fluoride.

WARNINGS

AS IN THE CASE OF ALL MEDICATIONS, KEEP OUT OF THE REACH OF CHILDREN. This tablet should be chewed. This product, as with all chewable tablets, are not recommended for children under the age of 4 due to risk of choking.

PRECAUTIONS

The suggested dose of MultiVitamin with Fluoride Chewable Tablets should not be exceeded, since dental fluorosis may result from continued ingestion of large amounts of fluoride.

Before recommending MultiVitamin with Fluoride Chewable Tablets

1. Determine the fluoride content of the drinking water from all major sources.

2. Make sure the child is not receiving significant amounts of fluoride from other sources such as medications and swallowed toothpaste.

3. Periodically check to make sure that the child does not develop significant dental fluorosis.

ADVERSE REACTIONS

Allergic rash and other idiosyncrasies have been rarely reported.

To report SUSPECTED ADVERSE REACTIONS, contact H2-Pharma, LLC at 1 (866) 592-6438 or FDA at 1 (800) 332-1088 or via the web at www.fda.gov/medwatch/index.html for voluntary reporting of adverse reactions.

DOSAGE AND ADMINISTRATION

One tablet daily or as directed by a physician.

HOW SUPPLIED

MultiVitamin with Fluoride Chewable Tablets 0.25 mg are available as orange chewable tablets imprinted with "155" in 100 tablet bottles.

MultiVitamin with Fluoride Chewable Tablets 0.5 mg are available as orange chewable tablets imprinted with "156" in 100 tablet bottles.

MultiVitamin with Fluoride Chewable Tablets 1.0 mg are available as orange chewable tablets imprinted with "157" in 100 tablet bottles.

STORAGE

Store at controlled room temperature 20°C-25°C (68°-77°F), excursions permitted between 15°-30°C (59°-86°F) [See USP].

Tamper Evident

Do not use if seal under cap is torn, broken or missing.

HEALTH CLAIM

Distributed by:
H2-Pharma, LLC
Montgomery, AL 36117

PRINCIPAL DISPLAY PANEL - 0.25 mg Tablet Bottle Label

61269-155-01

MultiVitamin
with Fluoride
Chewable Tablets

0.25 mg

MultiVitamin and Fluoride Supplement

Dietary Supplement
Orange Flavor

100 Tablets

H^2 pharma

PRINCIPAL DISPLAY PANEL - 0.5 mg Tablet Bottle Label

61269-156-01

MultiVitamin
with Fluoride
Chewable Tablets

0.5 mg

MultiVitamin and Fluoride Supplement

Dietary Supplement
Orange Flavor

100 Tablets

H^2 pharma

PRINCIPAL DISPLAY PANEL - 1 mg Tablet Bottle Label

61269-157-01

MultiVitamin
with Fluoride
Chewable Tablets

1 mg

MultiVitamin and Fluoride Supplement

Dietary Supplement
Orange Flavor

100 Tablets

H^2 pharma